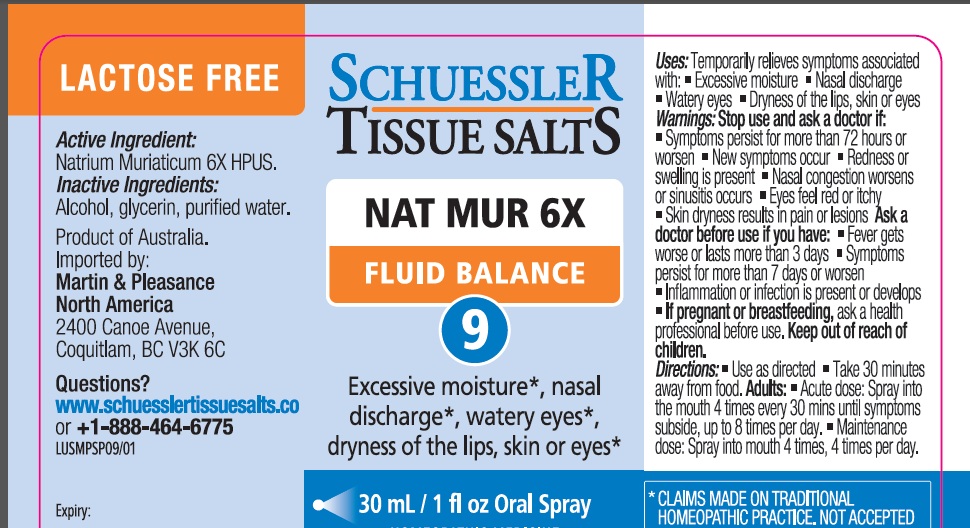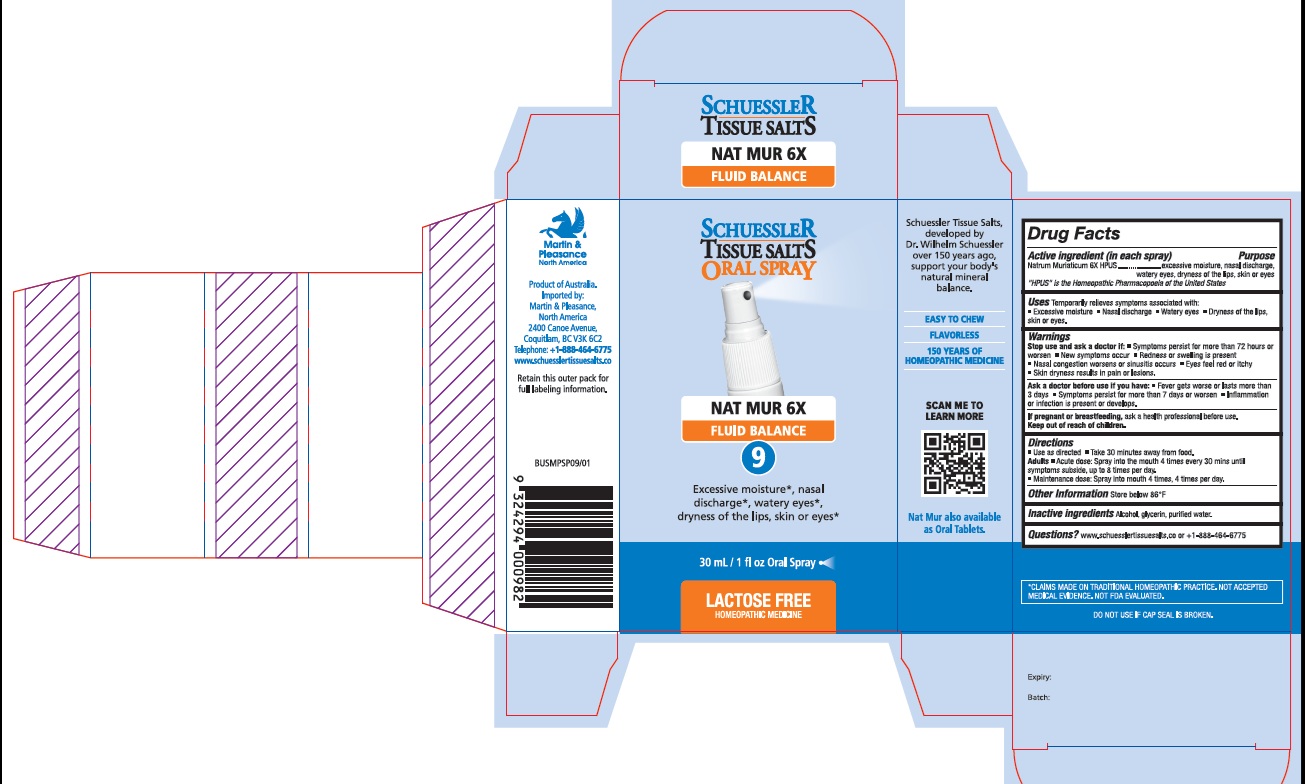 DRUG LABEL: Schuessler Tissue Salts Nat Mur Fluid Balance 9
NDC: 84999-009 | Form: SPRAY
Manufacturer: Martin & Pleasance Pty Ltd
Category: homeopathic | Type: HUMAN OTC DRUG LABEL
Date: 20250707

ACTIVE INGREDIENTS: SODIUM CHLORIDE 6 [hp_X]/30 mL
INACTIVE INGREDIENTS: ALCOHOL; GLYCERIN; WATER

Active ingredient (in each spray) Purpose

Natrum Muriaticum 6X HPUS excessive moisture, nasal discharge,watery eyes, dryness of the lips, skin or eyes

“ HPUS” is the Homeopathic Pharmacopoeia of the United States

Uses

Temporarily relieves symptoms associated with:

- Excessive moisture
- Nasal discharge
- Watery eyes
- Dryness of the lips, skin or eyes.

Warnings

Stop use and ask a doctor if:

- Symptoms persist for more than 72 hours or worsen
- New symptoms occur
- Redness or swelling is present
- Nasal congestion worsens or sinusitis occurs
- Eyes feel red or itchy
- Skin dryness results in pain or lesions.

Ask a doctor before use if you have:

- Fever gets worse or lasts more than 3 days
- Symptoms persist for more than 7 days or worsen
- Inflammation or infection is present or develops.

If pregnant or breastfeeding, ask a health professional before use. Keep out of reach of children.

Directions

- Use as directed
- Take 30 minutes away from food.

Adults

- Acute dose: Spray into the mouth 4 times every 30 mins until symptoms subside, up to 8 times per day.
- Maintenance dose: Spray into mouth 4 times, 4 times per day.

Other Information

Store below 86°F

Inactive Ingredients

Alcohol, Glycerin, Purified Water

Questions?www.schuesslertissuesalts.co or + 1-888-464-6775